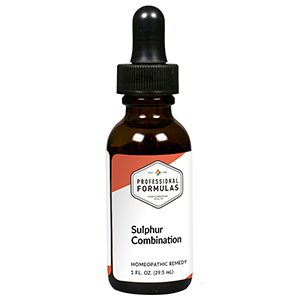 DRUG LABEL: Sulphur Combination
NDC: 63083-9247 | Form: LIQUID
Manufacturer: Professional Complementary Health Formulas
Category: homeopathic | Type: HUMAN OTC DRUG LABEL
Date: 20190815

ACTIVE INGREDIENTS: ASCLEPIAS TUBEROSA FLOWERING TOP 6 [hp_X]/29.5 mL; SULFUR 6 [hp_X]/29.5 mL; BRYONIA ALBA ROOT 10 [hp_X]/29.5 mL; SOLANUM DULCAMARA WHOLE 10 [hp_X]/29.5 mL
INACTIVE INGREDIENTS: ALCOHOL; WATER

R247

ACTIVE INGREDIENTS

Asclepias tuberosa 6X, 10X, 30X
Sulphur 6X, 10X
Bryonia 10X, 30X
Dulcamara 10X, 30X

QUESTIONS

Professional Formulas

PO Box 2034 Lake Oswego, OR 97035

INDICATIONS

Temporarily reduces runny nose, chills, sweats, sore throat, minor aches and pains in the muscles or joints, or occasional headache.*

PURPOSE

*Claims based on traditional homeopathic practice, not accepted medical evidence. Not FDA evaluated.

WARNINGS

Persistent symptoms may be a sign of a serious condition. If symptoms persist or are accompanied by a fever, rash, or persistent headache, consult a doctor. Keep out of the reach of children. In case of overdose, get medical help or contact a poison control center right away. If pregnant or breastfeeding, ask a healthcare professional before use.

Keep out of the reach of children.

PREGNANCY OR BREAST FEEDING

If pregnant or breastfeeding, ask a healthcare professional before use.

DIRECTIONS

Place drops under tongue 30 minutes before/after meals. Adults and children 12 years and over: Take 10 drops up to 3 times per day. Consult a physician for use in children under 12 years of age.

OTHER INFORMATION

Tamper resistant. If seal is broken, do not use. After opening, close container tightly and store at room temperature away from heat.

INACTIVE INGREDIENTS

40% ethanol, purified water.

LABEL

Est 1985

Professional Formulas

Complementary Health

Sulphur Combination

Homeopathic Remedy

1 FL. OZ. (29.5 mL)